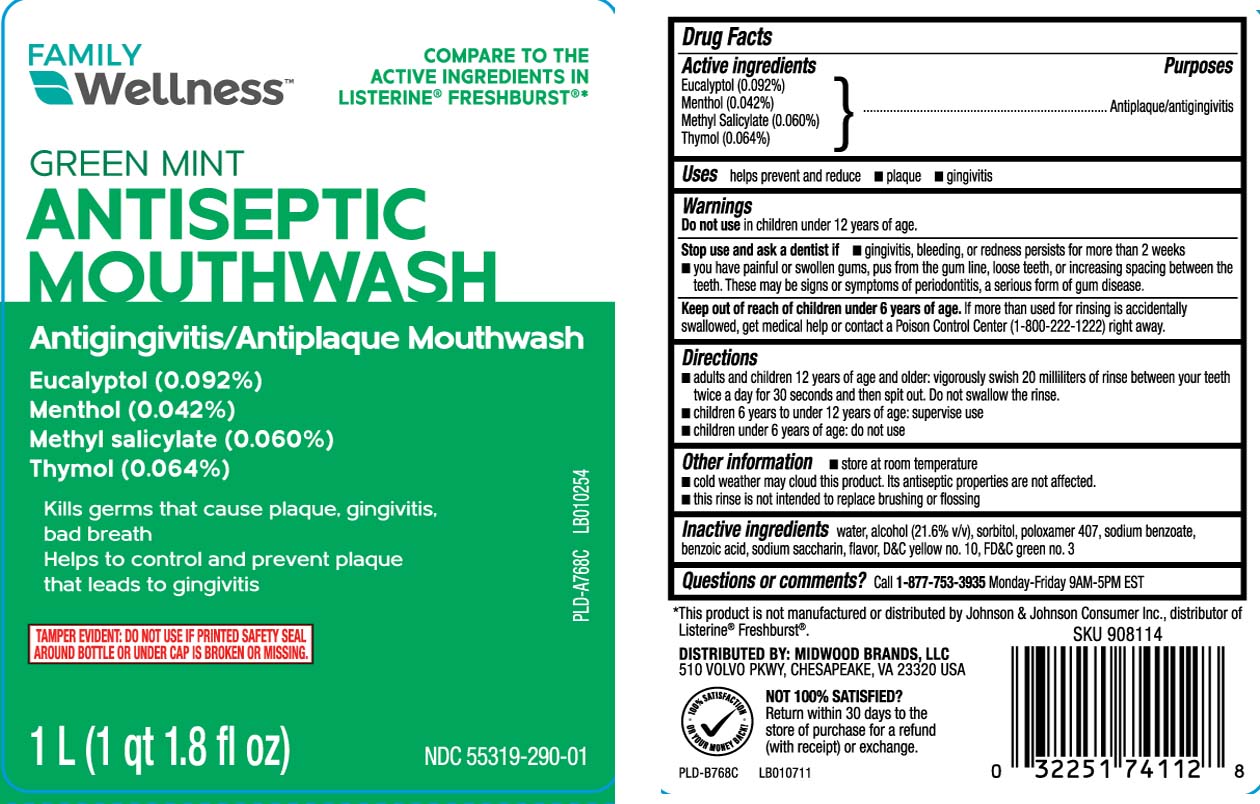 DRUG LABEL: Antiseptic
NDC: 55319-290 | Form: LIQUID
Manufacturer: Family Dollar (FAMILY WELLNESS)
Category: otc | Type: HUMAN OTC DRUG LABEL
Date: 20251105

ACTIVE INGREDIENTS: EUCALYPTOL 0.92 mg/1 mL; MENTHOL 0.42 mg/1 mL; METHYL SALICYLATE 0.6 mg/1 mL; THYMOL 0.64 mg/1 mL
INACTIVE INGREDIENTS: WATER; ALCOHOL; SORBITOL; POLOXAMER 407; SODIUM BENZOATE; BENZOIC ACID; SACCHARIN SODIUM; D&C YELLOW NO. 10; FD&C GREEN NO. 3

Kalaya Breath Refresh Antiseptic Oral Rinse-updated label for NDC

Active ingredient

Eucalyptol (0.092%)

Menthol (0.042%)

Methyl Salicylate (0.060%)

Thymol (0.064%)

Purposes

Antiplaque/antigingivitis

Uses

helps prevent and reduce

- plaque
- gingivitis

Warning

Do not use

in children under 12 years of age.

Stop use and ask a dentist

- gingivitis, bleeding, or redness persists for more than 2 weeks
- you have painful or swollen gums, pus from the gum line, loose teeth, or increasing spacing between the teeth. These may be signs or symptoms of periodontitis, a serious form of gum disease.

Keep out of reach of children under 6 years of age

If more than used for rinsing is accidentally swallowed, get medical help or contact a Poison Control Center (1-800-222-1222) right away

Directions

- adults and children 12 years of age and older: vigorously swish 20 milliliters of rinse between your teeth twice a day for 30 seconds and then spit out. Do not swallow the rinse.
- children 6 years to under 12 years of age: supervise use
- children under 6 years of age: do not use

Other information

- store at room temperature
- cold weather may cloud this product. Its antiseptic properties are not affected.
- this rinse is not intended to replace brushing or flossing

Inactive ingredients

water, alcohol (21.6% v/v), sorbitol, poloxamer 407, sodium benzoate, benzoic acid, sodium saccharin, flavor, D&C yellow no. 10, FD&C green no. 3

Questions or comments

Call 1-877-753-3935 Monday-Friday 9AM-5PM EST

Principal display panel

*Compare to the active ingredient in Listerine® Freshburst®

GREEN MINT

ANTISEPTIC

MOUTHWASH

Antigingivitis/Antiplaque Mouthwash

Eucalyptol (0.092%)

Menthol (0.042%)

Methyl salicylate (0.060%)

Thymol (0.064%)

Kill germs that cause plaque, gingivitis, bad breath

Helps to control and prevent plaque that leads to gingivitis

GREEN MINT

L (qt fl oz)

*This product is not manufactured or distributed by Johnson & Johnson Consumer Inc., distributor of Listerine® Freshburst®.

TAMPER EVIDENT: DO NOT USE IF PRINTED SAFETY SEAL AROUND BOTTLE OR UNDER CAP IS BROKEN OR MISSING.

DISTRIBUTED BY: MIDWOOD BRANDS, LLC

510 VOLVO PKWY, CHESAPEAKE, VA 23320 USA

Package label

FAMILY WELLNESS Green Mint Antiseptic Mouthwash